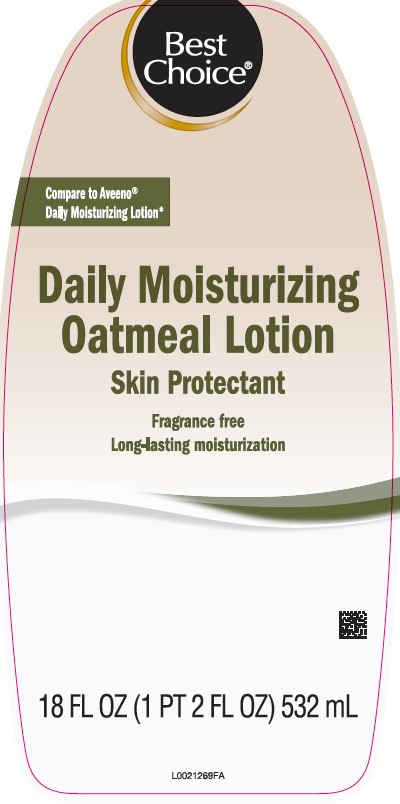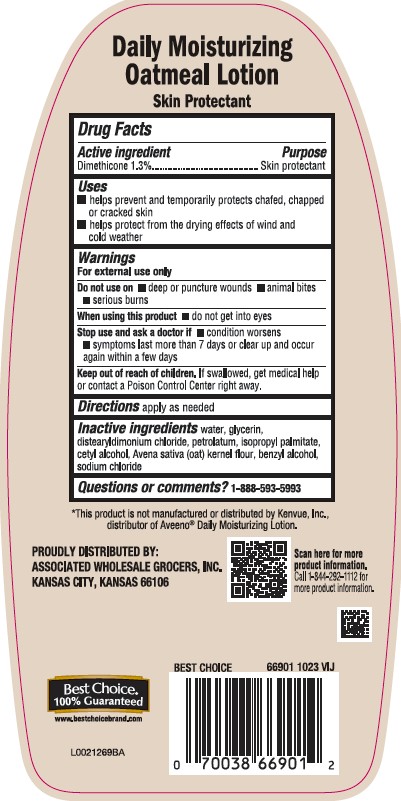 DRUG LABEL: Daily Moisturizing
NDC: 63941-620 | Form: LOTION
Manufacturer: Valu Merchandisers Company
Category: otc | Type: HUMAN OTC DRUG LABEL
Date: 20260216

ACTIVE INGREDIENTS: DIMETHICONE 13 mg/100 mL
INACTIVE INGREDIENTS: WATER; GLYCERIN; DISTEARYLDIMONIUM CHLORIDE; PETROLATUM; ISOPROPYL PALMITATE; CETYL ALCOHOL; OATMEAL; BENZYL ALCOHOL; SODIUM CHLORIDE

Best Choice 619.003/619AC
Daily Moisturizing Lotion

Active ingredient

Dimethicone 1.3%

Claims

Daily Moisturizing Oatmeal Lotion

Skin Protectant

Purpose

Skin Protectant

Uses

- helps prevent and temporarily protects chafed, chapped or cracked skin
- helps protect from the drying effects of wind and cold weather

Warnings

For external use only

Do Not Use

- on deep or puncture wounds
- animal bites
- serious burns

When using this product

- do not get into eyes

Stop use and ask a doctor if

- condition worsens
- symptoms last more than 7 days or clear up and occur again within a few days

Keep out of reach of children

If swallowed, get medical help or contact a Poison Control Center right away.

Directions

apply as needed

Inactive ingredients

water, glycerin, distearyldimonium chloride, petrolatum, isopropyl palmitate, cetyl alcohol, Avena sativa (oat) kernel flour, benzyl alcohol, sodium chloride

Questions or comments?

1-888-593-5993

Disclaimer

*This product is not manufactured or distributed by Kenvue, Inc. distributor of Aveeno®Daily Moisturizing Lotion.

Adverse reaction

PROUDLY DISTRIBUTED BY:

ASSOCIATED WHOLESALE GROCERS, INC.

KANSAS CITY, KANSAS 66106

Scan here for more product information.

Call 1-844-292-1112 for more porduct information.

Best Choice®

100% Guaranteed

www.bestchoicebrand.com

Principal display panel

Best Choice®

Compare to Aveeno®Daily Moisturizing Lotion*

Daily Moisturizing Oatmeal Lotion

Skin Protectant

Fragrance free

Long-lasting moisturization

18 FL OZ (1 PT 2 FL OZ) 532 mL